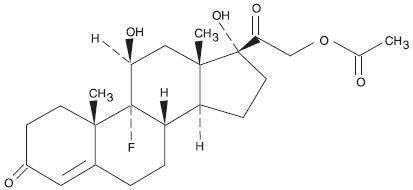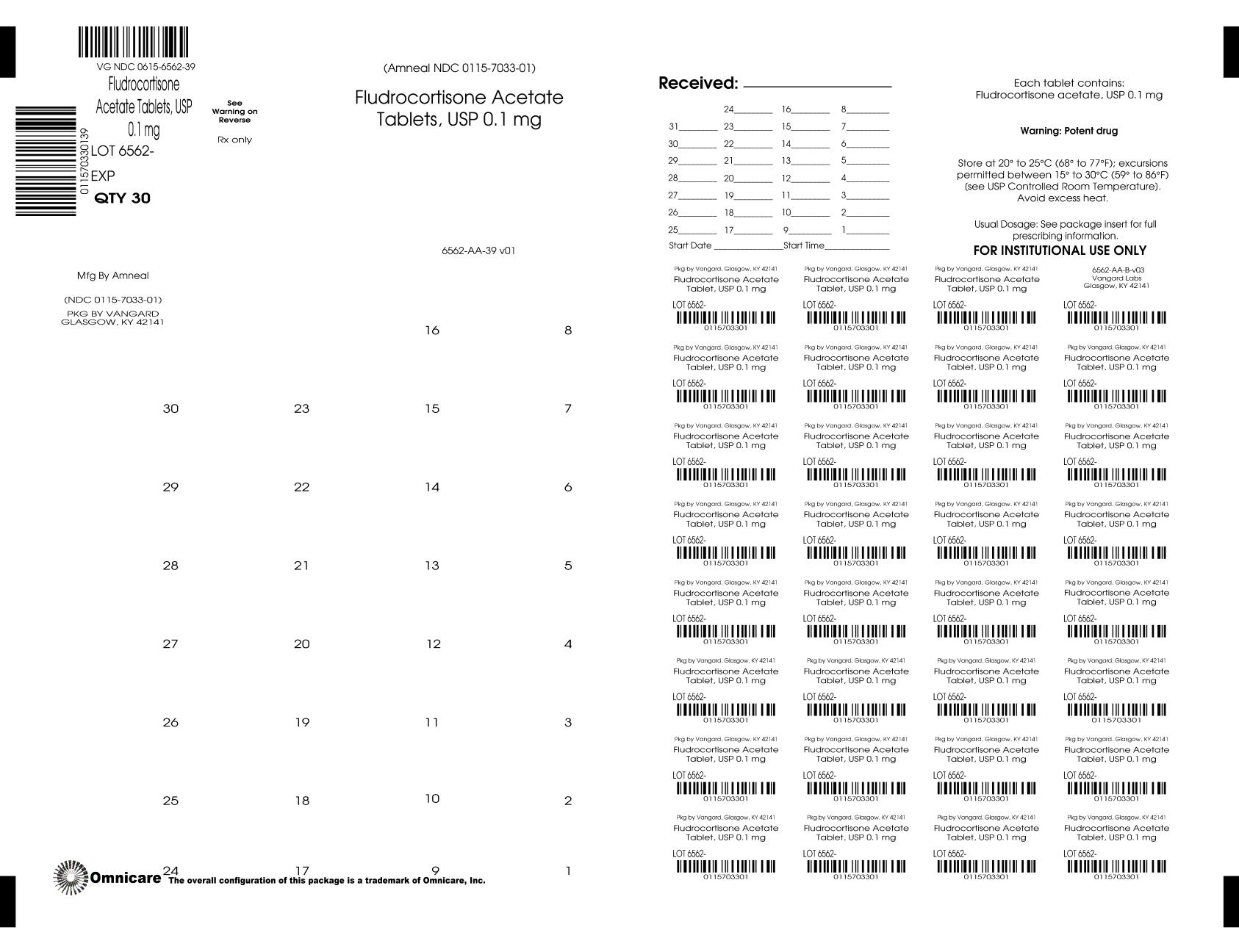 DRUG LABEL: Fludrocortisone Acetate
NDC: 0615-6562 | Form: TABLET
Manufacturer: NCS HealthCare of KY, LLC dba Vangard Labs
Category: prescription | Type: HUMAN PRESCRIPTION DRUG LABEL
Date: 20260227

ACTIVE INGREDIENTS: FLUDROCORTISONE ACETATE 0.1 mg/1 1
INACTIVE INGREDIENTS: CROSCARMELLOSE SODIUM; LACTOSE MONOHYDRATE; MAGNESIUM STEARATE; CELLULOSE, MICROCRYSTALLINE

Fludrocortisone Acetate Tablets, USP
(0.1 mg)

Rx only

DESCRIPTION

Fludrocortisone acetate tablets USP, 0.1 mg contain fludrocortisone acetate, USP a synthetic adrenocortical steroid possessing very potent mineralocorticoid properties and high glucocorticoid activity; it is used only for its mineralocorticoid effects. The chemical name for fludrocortisone acetate is 9-fluoro-11β, 17, 21-trihydroxypregn-4-ene-3, 20-dione 21-acetate; its structural formula is:

C23H31FO6 MW 422.49

Fludrocortisone acetate tablets USP, 0.1 mg are available for oral administration as scored tablets providing 0.1 mg fludrocortisone acetate, USP per tablet. Inactive ingredients: croscarmellose sodium NF, lactose monohydrate NF, magnesium stearate NF, and microcrystalline cellulose NF.

CLINICAL PHARMACOLOGY

Corticosteroids are thought to act at least in part, by controlling the rate of synthesis of proteins. Although there are a number of instances in which the synthesis of specific proteins is known to be induced by corticosteroids, the links between the initial actions of the hormones and the final metabolic effects have not been completely elucidated.

The physiologic action of fludrocortisone acetate is similar to that of hydrocortisone. However, the effects of fludrocortisone acetate, particularly on electrolyte balance, but also on carbohydrate metabolism, are considerably heightened and prolonged. Mineralocorticoids act on the distal tubules of the kidney to enhance the reabsorption of sodium ions from the tubular fluid into the plasma; they increase the urinary excretion of both potassium and hydrogen ions. The consequence of these three primary effects together with similar actions on cation transport in other tissues appear to account for the entire spectrum of physiological activities that are characteristic of mineralocorticoids. In small oral doses, fludrocortisone acetate produces marked sodium retention and increased urinary potassium excretion. It also causes a rise in blood pressure, apparently because of these effects on electrolyte levels.

In larger doses, fludrocortisone acetate inhibits endogenous adrenal cortical secretion, thymic activity, and pituitary corticotropin excretion; promotes the deposition of liver glycogen; and, unless protein intake is adequate, induces negative nitrogen balance.

The approximate plasma half-life of fludrocortisone (fluorohydrocortisone) is 3.5 hours or more and the biological half-life is 18 to 36 hours.

INDICATIONS AND USAGE

Fludrocortisone acetate tablets, 0.1 mg are indicated as partial replacement therapy for primary and secondary adrenocortical insufficiency in Addison’s disease and for the treatment of salt-losing adrenogenital syndrome.

CONTRAINDICATIONS

Corticosteroids are contraindicated in patients with systemic fungal infections and in those with a history of possible or known hypersensitivity to these agents.

WARNINGS

BECAUSE OF ITS MARKED EFFECT ON SODIUM RETENTION THE USE OF FLUDROCORTISONE ACETATE IN THE TREATMENT OF CONDITIONS OTHER THAN THOSE INDICATED HEREIN IS NOT ADVISED.

Corticosteroids may mask some signs of infection, and new infections may appear during their use. There may be decreased resistance and inability to localize infection when corticosteroids are used. If an infection occurs during fludrocortisone acetate therapy, it should be promptly controlled by suitable antimicrobial therapy.

Prolonged use of corticosteroids may produce posterior subcapsular cataracts, glaucoma with possible damage to the optic nerves, and may enhance the establishment of secondary ocular infections due to fungi or viruses.

Average and large doses of hydrocortisone or cortisone can cause elevation of blood pressure, salt and water retention, and increased excretion of potassium. These effects are less likely to occur with the synthetic derivatives except when used in large doses. However, since fludrocortisone acetate is a potent mineralocorticoid, both the dosage and salt intake should be carefully monitored in order to avoid the development of hypertension, edema or weight gain. Periodic checking of serum electrolyte levels is advisable during prolonged therapy; dietary salt restriction and potassium supplementation may be necessary. All corticosteroids increase calcium excretion.

Patients should not be vaccinated against smallpox while on corticosteroid therapy. Other immunization procedures should not be undertaken in patients who are on corticosteroids, especially on high dose, because of possible hazards of neurological complications and a lack of antibody response.

The use of fludrocortisone acetate in patients with active tuberculosis should be restricted to those cases of fulminating or disseminated tuberculosis in which the corticosteroid is used for the management of the disease in conjunction with an appropriate antituberculous regimen. If corticosteroids are indicated in patients with latent tuberculosis or tuberculin reactivity, close observation is necessary since reactivation of the disease may occur. During prolonged corticosteroid therapy these patients should receive chemoprophylaxis.

Children who are on immunosuppressant drugs are more susceptible to infections than healthy children. Chicken pox and measles, for example, can have a more serious or even fatal course in children on immunosuppressant corticosteroids. In such children, or in adults who have not had these diseases, particular care should be taken to avoid exposure. If exposed, therapy with variicella zoster immune globulin (VZIG) or pooled intravenous immunoglobulin (IVIG), as appropriate, may be indicated. If chicken pox develops, treatment with antiviral agents may be considered.

PRECAUTIONS

General

Adverse reactions to corticosteroids may be produced by too rapid withdrawal or by continued use of large doses.

To avoid drug-induced adrenal insufficiency, supportive dosage may be required in times of stress (such as trauma, surgery, or severe illness) both during treatment with fludrocortisone acetate and for a year afterwards.

There is an enhanced corticosteroid effect in patients with hypothyroidism and in those with cirrhosis.

Corticosteroids should be used cautiously in patients with ocular herpes simplex because of possible corneal perforation.

The lowest possible dose of corticosteroid should be used to control the condition being treated. A gradual reduction in dosage should be made when possible.

Psychic derangements may appear when corticosteroids are used. These may range from euphoria, insomnia, mood swings, personality changes, and severe depression to frank psychotic manifestations. Existing emotional instability or psychotic tendencies may also be aggravated by corticosteroids.

Aspirin should be used cautiously in conjunction with corticosteroids in patients with hypoprothrombinemia.

Corticosteroids should be used with caution in patients with nonspecific ulcerative colitis if there is a probability of impending perforation, abscess, or other pyogenic infection. Corticosteroids should also be used cautiously in patients with diverticulitis, fresh intestinal anastomoses, active or latent peptic ulcer, renal insufficiency, hypertension, osteoporosis, and myasthenia gravis.

Information for Patients

The physician should advise the patient to report any medical history of heart disease, high blood pressure, or kidney or liver disease and to report current use of any medicines to determine if these medicines might interact adversely with fludrocortisone acetate (see Drug Interactions).

Patients who are on immunosuppressant doses of corticosteroids should be warned to avoid exposure to chicken pox or measles and, if exposed, to obtain medical advice.

The patient’s understanding of his steroid-dependent status and increased dosage requirement under widely variable conditions of stress is vital. Advise the patient to carry medical identification indicating his dependence on steroid medication and, if necessary, instruct him to carry an adequate supply of medication for use in emergencies.

Stress to the patient the importance of regular follow-up visits to check his progress and the need to promptly notify the physician of dizziness, severe or continuing headaches, swelling of feet or lower legs, or unusual weight gain.

Advise the patient to use the medicine only as directed, to take a missed dose as soon as possible, unless it is almost time for the next dose, and not to double the next dose.

Inform the patient to keep this medication and all drugs out of the reach of children.

Laboratory Tests

Patients should be monitored regularly for blood pressure determinations and serum electrolyte determinations (see WARNINGS).

Drug Interactions

When administered concurrently, the following drugs may interact with adrenal corticosteroids.

Amphotericin B or potassium-depleting diuretics (benzothiadiazines and related drugs, ethacrynic acid and furosemide)—enhanced hypokalemia. Check serum potassium levels at frequent intervals; use potassium supplements if necessary (see WARNINGS).

Digitalis glycosides— enhanced possibility of arrhythmias or digitalis toxicity associated with hypokalemia. Monitor serum potassium levels; use potassium supplements if necessary.

Oral anticoagulants— decreased prothrombin time response. Monitor prothrombin levels and adjust anticoagulant dosage accordingly.

Antidiabetic drugs (oral agents and insulin)—diminished antidiabetic effect. Monitor for symptoms of hyperglycemia; adjust dosage of antidiabetic drug upward if necessary.

Aspirin— increased ulcerogenic effect; decreased pharmacologic effect of aspirin. Rarely salicylate toxicity may occur in patients who discontinue steroids after concurrent high-dose aspirin therapy. Monitor salicylate levels or the therapeutic effect for which aspirin is given; adjust salicylate dosage accordingly if effect is altered (see PRECAUTIONS, General).

Barbiturates, phenytoin, or rifampin—increased metabolic clearance of fludrocortisone acetate because of the induction of hepatic enzymes. Observe the patient for possible diminished effect of steroid and increase the steroid dosage accordingly.

Anabolic steroids (particularly C-17 alkylated androgens such as oxymetholone, methandrostenolone, norethandrolone, and similar compounds)—enhanced tendency toward edema. Use caution when giving these drugs together, especially in patients with hepatic or cardiac disease.

Vaccines—neurological complications and lack of antibody response (see WARNINGS).

Estrogen—increased levels of corticosteroid-binding globulin thereby increasing the bound (inactive) fraction; this effect is at least balanced by decreased metabolism of corticosteroids. When estrogen therapy is initiated, a reduction in corticosteroid dosage may be required, and increased amounts may be required when estrogen is terminated.

Drug/Laboratory Test Interactions

Corticosteroids may affect the nitrobluetetrazolium test for bacterial infection and produce false-negative results.

Carcinogenesis, Mutagenesis, Impairment of Fertility

Adequate studies have not been performed in animals to determine whether fludrocortisone acetate has carcinogenic or mutagenic activity or whether it affects fertility in males or females.

Pregnancy: Teratogenic Effects: Category C

Adequate animal reproduction studies have not been conducted with fludrocortisone acetate. However, many corticosteroids have been shown to be teratogenic in laboratory animals at low doses. Teratogenicity of these agents in man has not been demonstrated. It is not known whether fludrocortisone acetate can cause fetal harm when administered to a pregnant woman or can affect reproduction capacity. Fludrocortisone acetate should be given to a pregnant woman only if clearly needed.

Pregnancy: Nonteratogenic Effects

Infants born of mothers who have received substantial doses of fludrocortisone acetate during pregnancy should be carefully observed for signs of hypoadrenalism.

Maternal treatment with corticosteroids should be carefully documented in the infant’s medical records to assist in follow up.

Nursing Mothers

Corticosteroids are found in the breast milk of lactating women receiving systemic therapy with these agents. Caution should be exercised when fludrocortisone acetate is administered to a nursing woman.

Pediatric Use

Safety and effectiveness in children have not been established.

Growth and development of infants and children on prolonged corticosteroid therapy should be carefully observed.

ADVERSE REACTIONS

Most adverse reactions are caused by the drug’s mineralocorticoid activity (retention of sodium and water) and include hypertension, edema, cardiac enlargement, congestive heart failure, potassium loss, and hypokalemic alkalosis.

When fludrocortisone is used in the small dosages recommended, the glucocorticoid side effects often seen with cortisone and its derivatives are not usually a problem; however the following untoward effects should be kept in mind, particularly when fludrocortisone is used over a prolonged period of time or in conjunction with cortisone or a similar glucocorticoid.

Musculoskeletal—muscle weakness, steroid myopathy, loss of muscle mass, osteoporosis, vertebral compression fractures, aseptic necrosis of femoral and humeral heads, pathologic fracture of long bones, and spontaneous fractures.

Gastrointestinal—peptic ulcer with possible perforation and hemorrhage, pancreatitis, abdominal distention, and ulcerative esophagitis.

Dermatologic—impaired wound healing, thin fragile skin, bruising, petechiae and ecchymoses, facial erythema, increased sweating, subcutaneous fat atrophy, purpura, striae, hyperpigmentation of the skin and nails, hirsutism, acneiform eruptions and hives; reactions to skin tests may be suppressed.

Neurological—convulsions, increased intracranial pressure with papilledema (psuedo-tumor cerebri) usually after treatment, vertigo, headache, and severe mental disturbances.

Endocrine—menstrual irregularities; development of the cushingoid state; suppression of growth in children; secondary adrenocortical and pituitary unresponsiveness, particularly in times of stress (e.g., trauma, surgery, or illness); decreased carbohydrate tolerance; manifestations of latent diabetes mellitus; and increased requirements for insulin or oral hypoglycemic agents in diabetics.

Ophthalmic—posterior subcapsular cataracts, increased intraocular pressure, glaucoma, and exophthalmos.

Metabolic—hyperglycemia, glycosuria, and negative nitrogen balance due to protein catabolism.

Allergic Reactions—allergic skin rash, maculopapular rash, and urticaria.

Other adverse reactions that may occur following the administration of a corticosteroid are necrotizing angiitis, thrombophlebitis, aggravation or masking of infections, insomnia, syncopal episodes, and anaphylactoid reactions.

To report SUSPECTED ADVERSE REACTIONS, contact Amneal Pharmaceuticals at 1-877-835-5472 or FDA at 1-800-FDA-1088 or www.fda.gov/medwatch.

OVERDOSAGE

Development of hypertension, edema, hypokalemia, excessive increase in weight, and increase in heart size are signs of overdosage of fludrocortisone acetate. When these are noted, administration of drugs should be discontinued, after which the symptoms will usually subside within several days; subsequent treatment with fludrocortisone acetate should be with a reduced dose. Muscular weakness may develop due to excessive potassium loss and can be treated by administering a potassium supplement. Regular monitoring of blood pressure and serum electrolytes can help to prevent overdosage (see WARNINGS).

DOSAGE AND ADMINISTRATION

Dosage depends on the severity of the disease and the response of the patient. Patients should be continually monitored for signs that indicate dosage adjustment is necessary, such as remission or exacerbations of the disease and stress (surgery, infection, trauma) (see WARNINGS and PRECAUTIONS, General).

Addison's Disease

In Addison’s disease, the combination of fludrocortisone acetate tablets with a glucocorticoid such as hydrocortisone or cortisone provides substitution therapy approximating normal adrenal activity with minimal risks of unwanted effects.

The usual dose is 0.1 mg of fludrocortisone acetate tablets daily, although dosage ranging from 0.1 mg three times a week to 0.2 mg daily has been employed. In the event transient hypertension develops as a consequence of therapy, the dose should be reduced to 0.05 mg daily. Fludrocortisone acetate tablets are preferably administered in conjunction with cortisone (10 mg to 37.5 mg daily in divided doses) or hydrocortisone (10 mg to 30 mg daily in divided doses).

Salt-Losing Adrenogenital Syndrome

The recommended dosage for treating the salt-losing adrenogenital syndrome is 0.1 mg to 0.2 mg of fludrocortisone acetate tablets daily.

HOW SUPPLIED

Fludrocortisone Acetate Tablets USP, 0.1 mg — Each white to off-white, round, convex tablet debossed with a “7033” on one side and with a bisect on the other side.

They are available as follows:

Blistercards of 30: NDC 0615-6562-39

Store at 20° to 25°C (68° to 77°F); excursions permitted between 15° to 30°C (59° to 86°F) [see USP Controlled Room Temperature]. Avoid excessive heat.

Dispense in a tightly-closed, light-resistant container (USP).

Manufactured by:
Amneal Pharmaceuticals Pvt. Ltd.
Ahmedabad 382220, INDIA

Distributed by:
Amneal Pharmaceuticals LLC
Bridgewater, NJ 08807

Rev. 08-2024-03